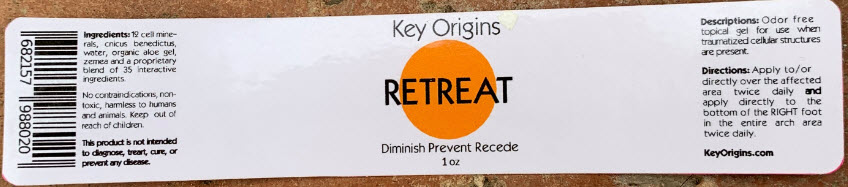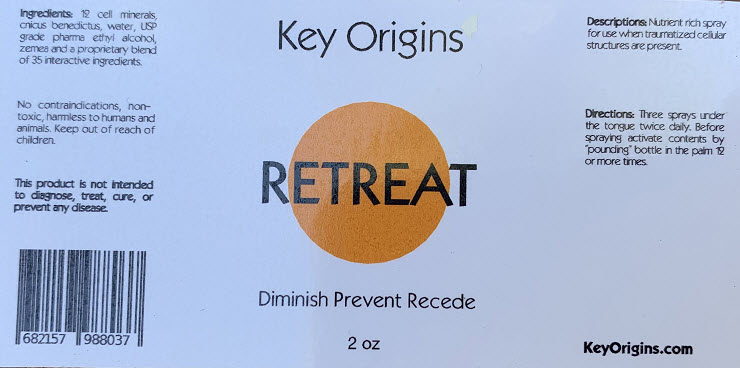 DRUG LABEL: Retreat
NDC: 72186-011 | Form: GEL
Manufacturer: Key Origins, Inc.
Category: homeopathic | Type: HUMAN OTC DRUG LABEL
Date: 20191226

ACTIVE INGREDIENTS: CALCIUM FLUORIDE 6 [hp_X]/1 mL; CALCIUM PHOSPHATE, UNSPECIFIED FORM 6 [hp_X]/1 mL; CALCIUM SULFATE, UNSPECIFIED FORM 6 [hp_X]/1 mL; FERROUS PHOSPHATE 6 [hp_X]/1 mL; MAGNESIUM PHOSPHATE, TRIBASIC, PENTAHYDRATE 6 [hp_X]/1 mL; POTASSIUM CHLORIDE 6 [hp_X]/1 mL; DIBASIC POTASSIUM PHOSPHATE 6 [hp_X]/1 mL; SODIUM CHLORIDE 6 [hp_X]/1 mL; SODIUM PHOSPHATE 6 [hp_X]/1 mL; SODIUM SULFATE 6 [hp_X]/1 mL; HYDRATED SILICA 6 [hp_X]/1 mL; CENTAUREA BENEDICTA 0.0231 mg/1 mL
INACTIVE INGREDIENTS: Water; Aloe Vera Leaf; Propanediol

Retreat

RETREAT GEL LABEL:

Ingredients

INACTIVE INGREDIENT

12 cell minerals, cnicus benedictus, water, organic aloe gel, zemea, and a proprietary blend of 35 interactive ingredients.

No contraindications, non-toxic, harmless to humans and animals.

WARNINGS

Keep out of reach of children.

This product is not intended to diagnose, treat, cure, or prevent any disease.

Descriptions

PURPOSE

Odor free topical gel for use when traumatized cellular structures are present.

Directions

Apply to/or directly over the affected area twice daily and apply directly to the bottom of the right foot in the entire arch area twice daily.

RETREAT SPRAY LABEL:

Ingredients

INACTIVE INGREDIENT

12 cell minerals, cnicus benedictus, water, USP grade pharma ethyl alcohol, zemea, and a proprietary blend of 35 interactive ingredients.

No contraindications, non-toxic, harmless to humans and animals.

WARNINGS

Keep out of reach of children.

This product is not intended to diagnose, treat, cure, or prevent any disease.

Descriptions

PURPOSE

Nutrient rich spray for use when traumatized cellular structures are present.

Directions

Three sprays under the tongue twice daily. Before spraying activate contents by "pounding" bottle in the palm 12 or more times.

PRINCIPAL DISPLAY PANEL - 1 oz Jar Label

Key Origins

RETREAT

Diminish Prevent Recede
1 oz

PRINCIPAL DISPLAY PANEL - 2 oz Bottle Spray

Key Origins

RETREAT

Diminish Prevent Recede

2 oz